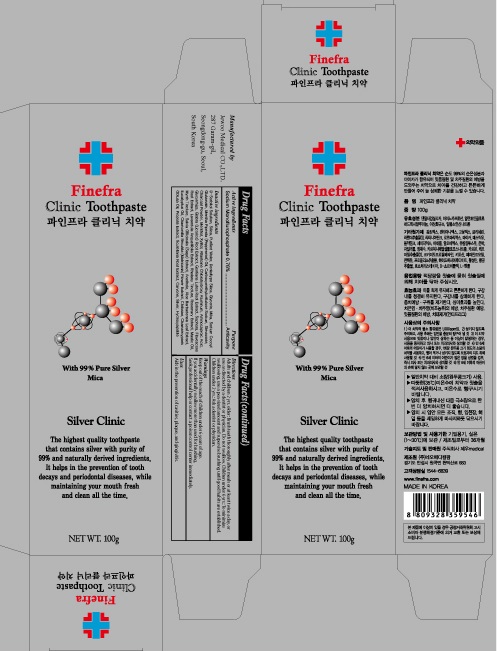 DRUG LABEL: Finefra Clinic Tooth
NDC: 69653-030 | Form: PASTE, DENTIFRICE
Manufacturer: Jewoo Medical Co,.Ltd
Category: otc | Type: HUMAN OTC DRUG LABEL
Date: 20181129

ACTIVE INGREDIENTS: Sodium Monofluorophosphate 0.76 g/100 g
INACTIVE INGREDIENTS: SORBITOL; SILICON DIOXIDE

ACTIVE INGREDIENT

Active ingredients: Sodium Monofluorophosphate 0.76%

INACTIVE INGREDIENT

Inactive ingredients:

D-Sorbitol Solution, Silica, Purified Water, Dentaltype Silica, Glycerin, Mika, Sodium Cocoyl Glutamate, Mentha Piperita (Peppermint) Oil, Carboxymethylcellulose Sodium, Stevioside, Charcoal Powder, Menthol, Xylitol, Allantoine Chlorohydroxy Aluminum, Aminocaproic Acid, Glycyrrhiza, Glabra (Licorice) Root Extract, Gentiana Lutea Root Extract, Sophora, Flavescens Root Extract, Lavandula Angustifolia Extract, Rhatany Tincture, Rosemary Extract, Mastic Oil, Myrrh Tincture, Salvia Officinalis (Sage) Extract, Anethole, Aloe Barbadensis Leaf Extract, Eucalyptus Oil, Chamomilla Recutita (Matricaria) Flower Extract, Chitosan, Chamaecyparis Obtusa Oil, Propolis Extract, Scutellaria Root Extract, Carvone, Silver, Hydroxyapatite

PURPOSE

Purpose: Anticavity

WARNINGS

Keep out of the reach of children under 6 years of age.

If you accidentally swallow more than used for brushing, Seek professional help or contact a poison control center immediately.

KEEP OUT OF REACH OF CHILDREN

Keep out of the reach of children under 6 years of age.

Uses

Aids in the prevention of cavities, plaque, and gingivitis.

Directions

Adults and children 2 yrs. older: Brush teeth thoroughly after meals or at least twice a day, or use as directed by a dentist or physician. Do not swallow. Children under 6 yrs.: To minimize swallowing, use a pea-sized amount and supervise brushing until good habits are established. Children under 2 yrs.: Ask a dentist or physician.